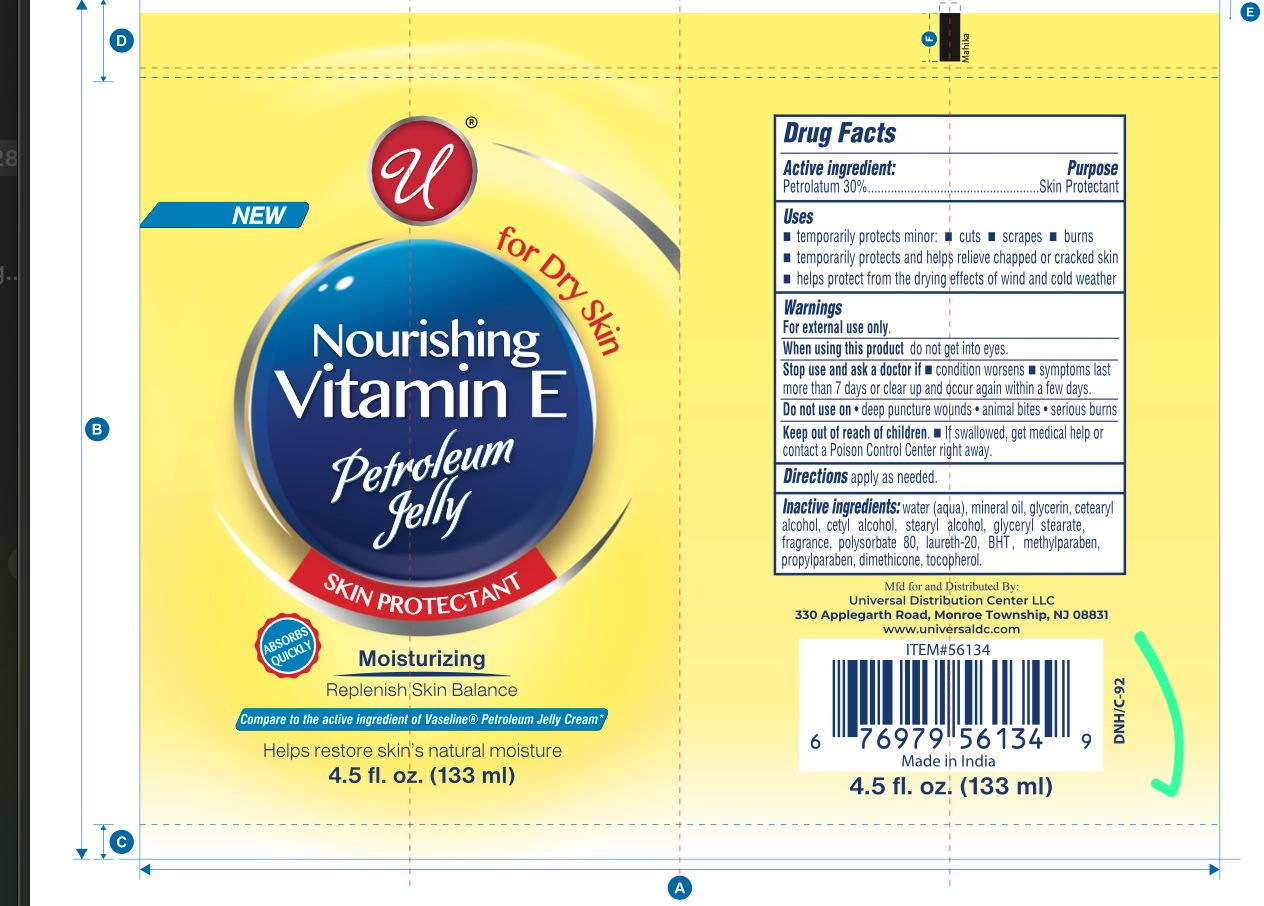 DRUG LABEL: Creamy Petroleum
NDC: 83650-103 | Form: JELLY
Manufacturer: Savvy Care & Cosmetics Pvt Ltd
Category: otc | Type: HUMAN OTC DRUG LABEL
Date: 20250704

ACTIVE INGREDIENTS: PETROLATUM 30 g/100 g
INACTIVE INGREDIENTS: BHT; WATER; POLYSORBATE 80; MINERAL OIL; METHYLPARABEN; PROPYLPARABEN; LAURETH-20; .ALPHA.-TOCOPHEROL ACETATE; GLYCERIN; CETYL ALCOHOL; CETEARYL ALCOHOL; DIMETHICONE; STEARYL ALCOHOL; GLYCERYL STEARATE

Creamy Petroleum Jelly

Active Ingredient

Petrolatum 30%

Purpose

Skin Protectant

Uses

- temporarily protects minor:
-
  - cuts
  - scrapes
  - burns
- temporarily protects and helps relieve chapped or cracked skin
- helps protect from the drying effects of wind and cold weather

Warnings

For external use only.

When using this product do not get into eyes.

Stop use and ask a doctor if

- condition worsens
- symptoms last more than 7 days or clear up and occur again within a few days

Do not use on

- deep puncture wounds
- animal bites
- serious burns

Keep out of reach of children.

If swallowed. get medical help or contact a Poison Control Center right away.

Directions

Apply as needed.

Inactive Ingredients

Aqua, Carbomer, Stearic Acid, Glyceryl Monostearate, Paraffinum Liquidum, Cetearyl Alcohol, Methylparaben, Propylparaben, Triethanolamine, Tocopheryl Acetate, Parfum